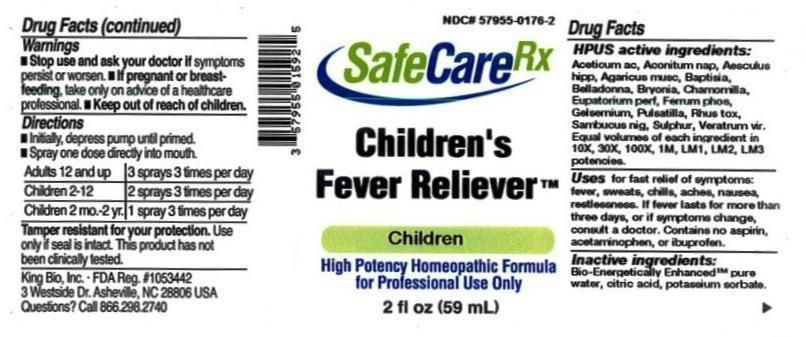 DRUG LABEL: Childrens Fever Reliever
NDC: 57955-0176 | Form: LIQUID
Manufacturer: King Bio INC.
Category: homeopathic | Type: HUMAN OTC DRUG LABEL
Date: 20150616

ACTIVE INGREDIENTS: ACETIC ACID 10 [hp_X]/59 mL; ACONITUM NAPELLUS 10 [hp_X]/59 mL; HORSE CHESTNUT 10 [hp_X]/59 mL; AMANITA MUSCARIA FRUITING BODY 10 [hp_X]/59 mL; BAPTISIA TINCTORIA ROOT 10 [hp_X]/59 mL; ATROPA BELLADONNA 10 [hp_X]/59 mL; BRYONIA ALBA ROOT 10 [hp_X]/59 mL; MATRICARIA RECUTITA 10 [hp_X]/59 mL; EUPATORIUM PERFOLIATUM FLOWERING TOP 10 [hp_X]/59 mL; FERROSOFERRIC PHOSPHATE 10 [hp_X]/59 mL; GELSEMIUM SEMPERVIRENS ROOT 10 [hp_X]/59 mL; PULSATILLA VULGARIS 10 [hp_X]/59 mL; TOXICODENDRON PUBESCENS LEAF 10 [hp_X]/59 mL; SAMBUCUS NIGRA FLOWERING TOP 10 [hp_X]/59 mL; SULFUR 10 [hp_X]/59 mL; VERATRUM VIRIDE ROOT 10 [hp_X]/59 mL
INACTIVE INGREDIENTS: WATER; ANHYDROUS CITRIC ACID; POTASSIUM SORBATE

Childrens Fever Reliever™

ACTIVE INGREDIENT

Drug Facts__________________________________________________________________________________________________________

HPUS active ingredients: Aceticum acidum, Aconitum napellus, Aesculus hippocastanum, Agaricus muscarius, Baptisia tinctoria, Belladonna, Bryonia alba, Chamomilla, Eupatoricum perfoliatum, Ferrum phosphoricum, Gelsemium sempervirens, Pulsatilla, Rhus toxicodendron, Sambucus nigra, Sulphur, Veratrum viride. Equal volumes of each ingredient in 10X, 30X, 100X, 1M, LM1, LM2, LM3 potencies.

INDICATIONS AND USAGE

Uses for fast relief of symptoms: fever, sweats, chills, aches, nausea, restlessness. If fever lasts for more than three days, or if symptoms change, consult a doctor. Contains no aspirin, acetaminophen, or ibuprofen.

Inactive Ingredients:

Bio-Energetically Enhanced™ pure water, citric acid and potassium sorbate.

Warnings

- Stop use and ask your doctor if symptoms persist or worsen.
- If pregnant or breast-feeding, take only on advice of a healthcare professional.

- Keep out of reach of children.

Directions

- Initially, depress pump until primed.
- Spray one dose directly into mouth.
- Adults 12 and up: 3 sprays 3 times per day.
- Children 2-12: 2 sprays 3 times per day.
- Children 2 mo.-2 yr: 1 spray 3 times per day.

OTHER SAFETY INFORMATION

Tamper resistant for your protection. Use only if safety seal is intact. This product has not been clinically tested.

PURPOSE

Uses for fast relief of symptoms:

- fever
- sweats
- chills
- aches
- nausea
- restlessness
- If fever lasts for more than three days, or if symptoms change, consult a doctor.
- Contains no aspirin, acetaminophen, or ibuprofen.